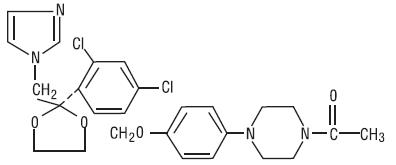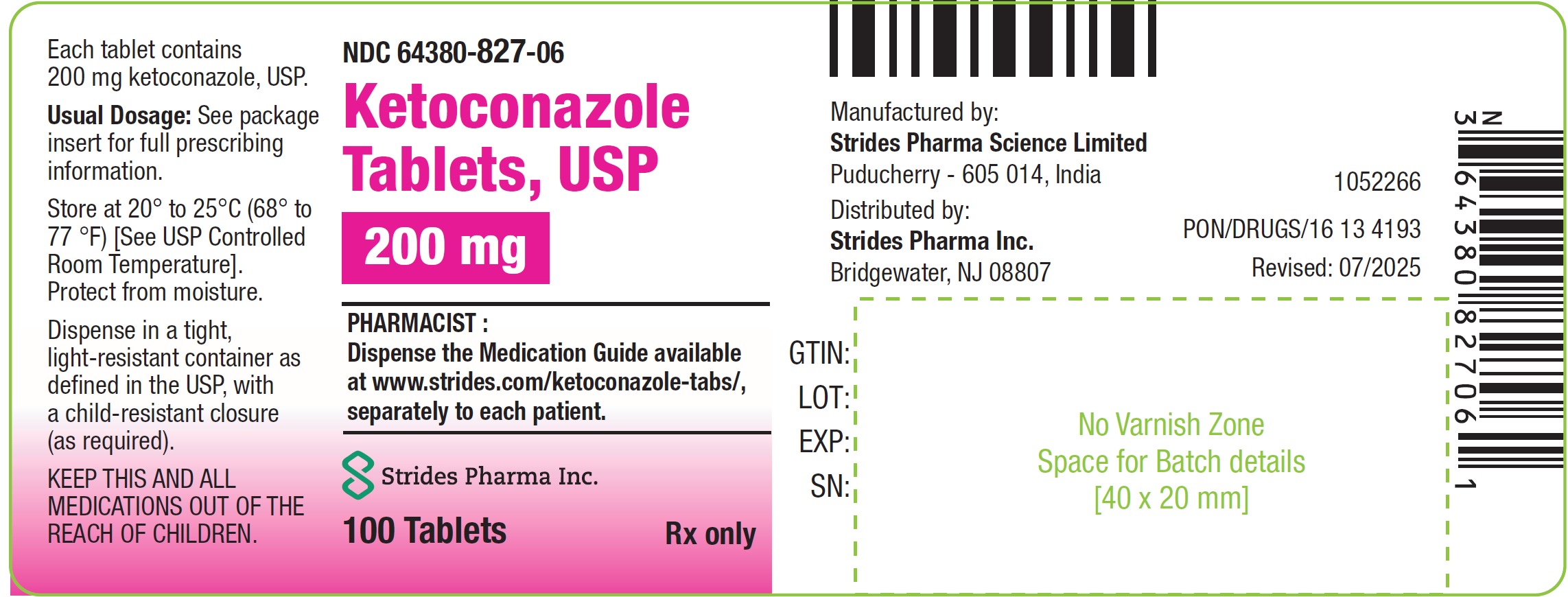 DRUG LABEL: KETOCONAZOLE
NDC: 64380-827 | Form: TABLET
Manufacturer: Strides Pharma Science Limited
Category: prescription | Type: HUMAN PRESCRIPTION DRUG LABEL
Date: 20251217

ACTIVE INGREDIENTS: KETOCONAZOLE 200 mg/1 1
INACTIVE INGREDIENTS: STARCH, CORN; LACTOSE MONOHYDRATE; MAGNESIUM STEARATE; CELLULOSE, MICROCRYSTALLINE; POVIDONE K30; SILICON DIOXIDE

KETOCONAZOLE TABLETS USP, 200 mg
Rx only

WARNING:

Because ketoconazole tablets have been associated with serious adverse reactions (see WARNINGS section), ketoconazole tablets are not indicated for treatment of onychomycosis, cutaneous dermatophyte infections, or Candida infections.

Ketoconazole tablets should be used only when other effective antifungal therapy is not available or tolerated and the potential benefits are considered to outweigh the potential risks.

Hepatotoxicity

Serious hepatotoxicity, including cases with a fatal outcome or requiring liver transplantation has occurred with the use of oral ketoconazole. Some patients had no obvious risk factors for liver disease. Patients receiving this drug should be informed by the physician of the risk and should be closely monitored. See WARNINGS section.

QT Prolongation and Drug Interactions Leading to QT Prolongation

Coadministration of the following drugs with ketoconazole is contraindicated: dofetilide, quinidine, pimozide, lurasidone, cisapride, methadone, disopyramide, dronedarone, ranolazine. Ketoconazole can cause elevated plasma concentrations of these drugs and may prolong QT intervals, sometimes resulting in life-threatening ventricular dysrhythmias such as torsades de pointes. See CONTRAINDICATIONS, WARNINGS, and PRECAUTIONS: Drug Interactions sections.

DESCRIPTION

Ketoconazole, USP is a synthetic broad-spectrum antifungal agent. Each tablet, for oral administration, contains 200 mg ketoconazole, USP base. In addition, each tablet contains the following inactive ingredients: colloidal silicon dioxide, corn starch, lactose monohydrate, magnesium stearate, microcrystalline cellulose, and povidone. Ketoconazole is (±)cis-1-Acetyl-4-[p-[[2-(2,4-dichlorophenyl)-2-(imidazol-1-ylmethyl)-1,3-dioxolan-4-yl]methoxy]phenyl]-piperazine and has the following structural formula:

C26H28Cl2N4O4 M.W. 531.44

Ketoconazole, USP is a white or almost white powder that is soluble in acids.

CLINICAL PHARMACOLOGY

Pharmacokinetics

Absorption

Ketoconazole is a weak dibasic agent and thus requires acidity for dissolution and absorption.

Mean peak plasma concentrations of approximately 3.5 mcg/mL are reached within 1 to 2 hours, following oral administration of a single 200 mg dose taken with a meal. Oral bioavailability is maximal when the tablets are taken with a meal.

Absorption of ketoconazole tablets is reduced in subjects with reduced gastric acidity, such as subjects taking medications known as acid neutralizing medicines (e.g. aluminum hydroxide) and gastric acid secretion suppressors (e.g. H2-receptor antagonists, proton pump inhibitors) or subjects with achlorhydria caused by certain diseases (see PRECAUTIONS: Drug Interactions). Absorption of ketoconazole under fasted conditions in these subjects is increased when ketoconazole tablets are administered with an acidic beverage (such as non-diet cola). After pretreatment with omeprazole, a proton pump inhibitor, the bioavailability of a single 200 mg dose of ketoconazole under fasted conditions was decreased to 17% of the bioavailability of ketoconazole administered alone. When ketoconazole was administered with non-diet cola after pretreatment with omeprazole, the bioavailability was 65% of that after administration of ketoconazole alone.

Distribution

In vitro, the plasma protein binding is about 99% mainly to the albumin fraction. Ketoconazole is widely distributed into tissues; however, only a negligible proportion reaches the cerebrospinal fluid.

Metabolism

Following absorption from the gastrointestinal tract, ketoconazole tablets are converted into several inactive metabolites. In vitro studies have shown that CYP3A4 is the major enzyme involved in the metabolism of ketoconazole. The major identified metabolic pathways are oxidation and degradation of the imidazole and piperazine rings, by hepatic microsomal enzymes. In addition, oxidative O-dealkylation and aromatic hydroxylation does occur. Ketoconazole has not been demonstrated to induce its own metabolism.

Elimination

Elimination from plasma is biphasic with a half-life of 2 hours during the first 10 hours and 8 hours thereafter.

Approximately 13% of the dose is excreted in the urine, of which 2 to 4% is unchanged drug. The major route of excretion is through the bile into the intestinal tract with about 57% being excreted in the feces.

Special Populations

Patients with Hepatic or Renal Impairment

In patients with hepatic or renal impairment, the overall pharmacokinetics of ketoconazole was not significantly different when compared with healthy subjects.

Pediatric Patients

Limited pharmacokinetic data are available on the use of ketoconazole tablets in the pediatric population.

Measurable ketoconazole plasma concentrations have been observed in pre-term infants (single or daily doses of 3 to 10 mg/kg) and in pediatric patients 5 months of age and older (daily doses of 3 to 13 mg/kg) when the drug was administered as a suspension, tablet or crushed tablet. Limited data suggest that absorption may be greater when the drug is administered as a suspension compared to a crushed tablet. Conditions that raise gastric pH may lower or prevent absorption (see PRECAUTIONS: Drug Interactions). Maximum plasma concentrations occurred 1 to 2 hours after dosing and were in the same general range as those seen in adults who received a 200 to 400 mg dose.

Electrocardiogram

Pre-clinical electrophysiological studies have shown that ketoconazole inhibits the rapidly activating component of the cardiac delayed rectifier potassium current, prolongs the action potential duration, and may prolong the QTC interval. Data from some clinical PK/PD studies and drug interaction studies suggest that oral dosing with ketoconazole at 200 mg twice daily for 3 to 7 days can result in an increase of the QTC interval: a mean maximum increase of about 6 to 12 msec was seen at ketoconazole peak plasma concentrations about 1 to 4 hours after ketoconazole administration.

MICROBIOLOGY

Mechanism of Action

Ketoconazole blocks the synthesis of ergosterol, a key component of the fungal cell membrane, through the inhibition of cytochrome P-450 dependent enzyme lanosterol 14α-demethylase responsible for the conversion of lanosterol to ergosterol in the fungal cell membrane. This results in an accumulation of methylated sterol precursors and a depletion of ergosterol within the cell membrane thus weakening the structure and function of the fungal cell membrane.

Activity In Vitro & In Vivo

Ketoconazole tablets are active against clinical infections with Blastomyces dermatitidis, Coccidioides immitis, Histoplasma capsulatum, Paracoccidioides brasiliensis.

INDICATIONS & USAGE

Ketoconazole tablets are not indicated for treatment of onychomycosis, cutaneous dermatophyte infections, or Candida infections.

Ketoconazole tablets should be used only when other effective antifungal therapy is not available or tolerated and the potential benefits are considered to outweigh the potential risks.

Ketoconazole tablets are indicated for the treatment of the following systemic fungal infections in patients who have failed or who are intolerant to other therapies: blastomycosis, coccidioidomycosis, histoplasmosis, chromomycosis, and paracoccidioidomycosis. Ketoconazole tablets should not be used for fungal meningitis because it penetrates poorly into the cerebrospinal fluid.

CONTRAINDICATIONS

Drug Interactions

Coadministration of a number of CYP3A4 substrates such as dofetilide, quinidine cisapride and pimozide is contraindicated with ketoconazole tablets. Coadministration with ketoconazole can cause elevated plasma concentrations of these drugs and may increase or prolong both therapeutic and adverse effects to such an extent that a potentially serious adverse reaction may occur. For example, increased plasma concentrations of some of these drugs can lead to QT prolongation and sometimes resulting in life-threatening ventricular tachyarrhythmias including occurrences of torsade de pointes, a potentially fatal arrhythmia. Coadministration of ketoconazole tablets with lurasidone is contraindicated since it may result in an increase in lurasidone exposure and the potential for serious adverse reactions. (see PRECAUTIONS: Drug Interactions).

Additionally, the following other drugs are contraindicated with ketoconazole tablets: methadone, disopyramide, dronedarone, ergot alkaloids such as dihydroergotamine, ergometrine, ergotamine, methylergometrine, irinotecan, lurasidone, oral midazolam, alprazolam, triazolam, felodipine, nisoldipine, ranolazine, tolvaptan, eplerenone, lovastatin, simvastatin and colchicine (see PRECAUTIONS: Drug Interactions).

Enhanced Sedation

Coadministration of ketoconazole tablets with oral midazolam, oral triazolam or alprazolam has resulted in elevated plasma concentrations of these drugs. This may potentiate and prolong hypnotic and sedative effects, especially with repeated dosing or chronic administration of these agents. Concomitant administration of ketoconazole tablets with oral triazolam, oral midazolam or alprazolam is contraindicated (see PRECAUTIONS: Drug Interactions).

Myopathy

Coadministration of CYP3A4 metabolized HMG-CoA reductase inhibitors such as simvastatin, and lovastatin is contraindicated with ketoconazole tablets (see PRECAUTIONS: Drug Interactions).

Ergotism

Concomitant administration of ergot alkaloids such as dihydroergotamine and ergotamine with ketoconazole tablets is contraindicated (see PRECAUTIONS: Drug Interactions).

Liver Disease

The use of ketoconazole tablets are contraindicated in patients with acute or chronic liver disease.

Hypersensitivity

Ketoconazole tablets are contraindicated in patients who have shown hypersensitivity to the drug.

WARNINGS

Because of the serious adverse reactions that have been reported in association with ketoconazole, including fatal hepatotoxicity, ketoconazole tablets are not indicated for treatment of onychomycosis, cutaneous dermatophyte infections, or Candida infections.

Ketoconazole tablets should be used only when other effective antifungal therapy is not available or tolerated and the potential benefits are considered to outweigh the potential risks.

Hepatotoxicity

Serious hepatotoxicity, including cases with a fatal outcome or requiring liver transplantation, has occurred with the use of oral ketoconazole. Some patients had no obvious risk factors for liver disease. Serious hepatotoxicity was reported both by patients receiving high doses for short treatment durations and by patients receiving low doses for long durations.

The hepatic injury has usually, but not always, been reversible upon discontinuation of ketoconazole tablets treatment. Cases of hepatitis have been reported in children.

At baseline, obtain laboratory tests (such as SGGT, alkaline phosphatase, ALT, AST, total bilirubin (TBL), Prothrombin Time (PT), International Normalization Ratio (INR), and testing for viral hepatitides). Patients should be advised against alcohol consumption while on treatment. If possible, use of other potentially hepatotoxic drugs should be avoided in patients receiving ketoconazole tablets.

Prompt recognition of liver injury is essential. During the course of treatment, serum ALT should be monitored weekly for the duration of treatment. If ALT values increase to a level above the upper limit of normal or 30 percent above baseline, or if the patient develops symptoms, ketoconazole treatment should be interrupted and a full set of liver tests should be obtained. Liver tests should be repeated to ensure normalization of values. Hepatotoxicity has been reported with restarting oral ketoconazole (rechallenge). If it is decided to restart oral ketoconazole, monitor the patient frequently to detect any recurring liver injury from the drug.

QT Prolongation and Drug Interactions Leading to QT Prolongation

Ketoconazole can prolong the QT interval. Coadministration of the following drugs with ketoconazole is contraindicated: dofetilide, quinidine, pimozide, lurasidone, cisapride, methadone, disopyramide, dronedarone, ranolazine. Ketoconazole can cause elevated plasma concentrations of these drugs which may prolong the QT interval, sometimes resulting in life-threatening ventricular dysrhythmias such as torsades de pointes.

Adrenal Insufficiency

Ketoconazole tablets decrease adrenal corticosteroid secretion at doses of 400 mg and higher. This effect is not shared with other azoles. The recommended dose of 200 mg to 400 mg daily should not be exceeded.

Adrenal function should be monitored in patients with adrenal insufficiency or with borderline adrenal function and in patients under prolonged periods of stress (major surgery, intensive care, etc.).

Adverse Reactions Associated with Unapproved Uses

Ketoconazole has been used in high doses for the treatment of advanced prostate cancer and for Cushing's syndrome when other treatment options have failed. The safety and effectiveness of ketoconazole have not been established in these settings and the use of ketoconazole for these indications is not approved by FDA.

In a clinical trial involving 350 patients with metastatic prostatic cancer, eleven deaths were reported within two weeks of starting treatment with high doses of ketoconazole tablets (1200 mg/day). It is not possible to ascertain from the information available whether death was related to ketoconazole therapy or adrenal insufficiency in these patients with serious underlying disease.

Hepatoxicity, including fatal cases and cases requiring liver transplantation, have been reported in patients who received ketoconazole for treatment of onychomycosis, cutaneous dermatophyte infections, or Candida infections.

Hypersensitivity

Anaphylaxis has been reported after the first dose. Several cases of hypersensitivity reactions including urticaria have also been reported.

PRECAUTIONS

General

Ketoconazole tablets have been demonstrated to lower serum testosterone. Once therapy with ketoconazole has been discontinued, serum testosterone levels return to baseline values. Testosterone levels are impaired with doses of 800 mg per day and abolished by 1600 mg per day. Clinical manifestations of decreased testosterone concentrations may include gynecomastia, impotence and oligospermia.

Information for Patients

Patients should be instructed to report any signs and symptoms which may suggest liver dysfunction so that appropriate biochemical testing can be done. Such signs and symptoms may include unusual fatigue, anorexia, nausea and/or vomiting, abdominal pain, jaundice, dark urine or pale stools (see WARNINGS section).

Drug Interactions

Ketoconazole is mainly metabolized through CYP3A4. Other substances that either share this metabolic pathway or modify CYP3A4 activity may influence the pharmacokinetics of ketoconazole. Similarly, ketoconazole may modify the pharmacokinetics of other substances that share this metabolic pathway. Ketoconazole is a potent CYP3A4 inhibitor and a P-glycoprotein inhibitor. When using concomitant medication, the corresponding label should be consulted for information on the route of metabolism and the possible need to adjust dosages.

Interaction studies have only been performed in adults. The relevance of the results from these studies in pediatric patients is unknown.

Drugs that may decrease ketoconazole plasma concentrations

Drugs that reduce the gastric acidity (e.g., acid neutralizing medicines such as aluminum hydroxide, or acid secretion suppressors such as H2-receptor antagonists and proton pump inhibitors) impair the absorption of ketoconazole from ketoconazole tablets. These drugs should be used with caution when coadministered with ketoconazole tablets:

- Ketoconazole tablets should be administered with an acidic beverage (such as non-diet cola) upon co-treatment with drugs reducing gastric acidity.
- Acid neutralizing medicines (e.g., aluminum hydroxide) should be administered at least 1 hour before or 2 hours after the intake of ketoconazole tablets.
- Upon coadministration, the antifungal activity should be monitored and the ketoconazole tablets dose increased as deemed necessary.

Coadministration of ketoconazole tablets with potent enzyme inducers of CYP3A4 may decrease the bioavailability of ketoconazole to such an extent that efficacy may be reduced. Examples include:

- Antibacterials: isoniazid, rifabutin (see also under 'Drugs that may have their plasma concentrations increased'), rifampicin.
- Anticonvulsants: carbamazepine (see also under 'Drugs that may have their plasma concentrations increased'), phenytoin.
- Antivirals: efavirenz, nevirapine.

Therefore, administration of potent enzyme inducers of CYP3A4 with ketoconazole tablets is not recommended. The use of these drugs should be avoided from 2 weeks before and during treatment with ketoconazole tablets, unless the benefits outweigh the risk of potentially reduced ketoconazole efficacy. Upon coadministration, the antifungal activity should be monitored and the ketoconazole tablets dose increased as deemed necessary.

Drugs that may increase ketoconazole plasma concentrations

Potent inhibitors of CYP3A4 (e.g., antivirals such as ritonavir, ritonavir-boosted darunavir and ritonavir-boosted fosamprenavir) may increase the bioavailability of ketoconazole. These drugs should be used with caution when coadministered with ketoconazole tablets.

Patients who must take ketoconazole tablets concomitantly with potent inhibitors of CYP3A4 should be monitored closely for signs or symptoms of increased or prolonged pharmacologic effects of ketoconazole, and the ketoconazole tablets dose should be decreased as deemed necessary. When appropriate, ketoconazole plasma concentrations should be measured.

Drugs that may have their plasma concentrations increased by ketoconazole

Ketoconazole can inhibit the metabolism of drugs metabolized by CYP3A4 and can inhibit the drug transport by P-glycoprotein, which may result in increased plasma concentrations of these drugs and/or their active metabolite(s) when they are administered with ketoconazole. These elevated plasma concentrations may increase or prolong both therapeutic and adverse effects of these drugs. CYP3A4- metabolized drugs known to prolong the QT interval may be contraindicated with ketoconazole tablets, since the combination may lead to ventricular tachyarrhythmias, including occurrences of torsade de pointes, a potentially fatal arrhythmia.

Examples of drugs that may have their plasma concentrations increased by ketoconazole presented by drug class with advice regarding coadministration with ketoconazole tablets:

Drug Class | Contraindicated | Not Recommended | Use with Caution | Comments
 | Under no circumstances should the drug be coadministered with ketoconazole tablets, and up to one week after discontinuation of treatment with ketoconazole. | The use of the drug should be avoided during and up to one week after discontinuation of treatment with ketoconazole tablets, unless the benefits outweigh the potentially increased risks of side effects. If coadministration cannot be avoided, clinical monitoring for signs or symptoms of increased or prolonged effects or side effects of the interacting drug is recommended, and its dosage should be reduced or interrupted as deemed necessary. When appropriate, plasma concentrations should be measured. The label of the coadministered drug should be consulted for information on dose adjustment and adverse effects. | Careful monitoring is recommended when the drug is coadministered with ketoconazole tablets. Upon coadministration, patients should be monitored closely for signs or symptoms of increased or prolonged effects or side effects of the interacting drug, and its dosage should be reduced as deemed necessary. When appropriate, plasma concentrations should be measured. The label of the coadministered drug should be consulted for information on dose adjustment and adverse effects .
Alpha Blockers |  | tamsulosin
Analgesics | methadone |  | alfentanil, buprenorphine IV and sublingual, fentanyl, oxycodone, sufentanil | Methadone: The potential increase in plasma concentrations of methadone when coadministered with ketoconazole tablets may increase the risk of serious cardiovascular events including QT prolongation and torsade de pointes, or respiratory or CNS depression [See CONTRAINDICATIONS .] Fentanyl: The potential increase in plasma concentrations of fentanyl when coadministered with ketoconazole tablets may increase the risk of potentially fatal respiratory depression. Sufentanil: No human pharmacokinetic data of an interaction with ketoconazole are available. In vitro data suggest that sufentanil is metabolized by CYP3A4 and so potentially increased sufentanil plasma concentrations would be expected when coadministered with ketoconazole tablets.
Antiarrhythmics | disopyramide, dofetilide, dronedarone, quinidine |  | digoxin | Disopyramide, dofetilide, dronedarone, quinidine: The potential increase in plasma concentrations of these drugs when coadministered with ketoconazole may increase the risk of serious cardiovascular events including QT prolongation. Digoxin: Rare cases of elevated plasma concentrations of digoxin have been reported. It is not clear whether this was due to the combination of therapy. It is, therefore, advisable to monitor digoxin concentrations in patients receiving ketoconazole.
Antibacterials |  | rifabutin | telithromycin | Rifabutin: see also under Drugs that may decrease ketoconazole plasma concentrations. Telithromycin: A multiple-dose interaction study with ketoconazole showed that Cmax of telithromycin was increased by 51% and AUC by 95%.
Anticoagulants and Antiplatelet Drugs |  | rivaroxaban | cilostazol, coumarins, dabigatran | Cilostazol: Concomitant administration of single doses of cilostazol 100 mg and ketoconazole 400 mg approximately doubled cilostazol concentrations and altered (increase/decrease) the concentrations of the active metabolites of cilostazol. Coumarins: Ketoconazole may enhance the anticoagulant effect of coumarin-like drugs, thus the anticoagulant effect should be carefully titrated and monitored. Dabigatran: In patients with moderate renal impairment (CrCL 50 mL/min to ≤ 80 mL/min), consider reducing the dose of dabigatran to 75 mg twice daily when it is coadministered with ketoconazole.
Anticonvulsants |  | carbamazepine |  | Carbamazepine: In vivo studies have demonstrated an increase in plasma carbamazepine concentrations in subjects concomitantly receiving ketoconazole. In addition, the bioavailability of ketoconazole may be reduced by carbamazepine.
Antidiabetics |  |  | repaglinide, saxagliptin
Antihelmintics and Antiprotozoals |  |  | praziquantel
Antimigraine Drugs | ergot alkaloids, such as dihydroergotamine, ergometrine (ergonovine), ergotamine, methylergometrine (methylergonovine) |  | eletriptan | Ergot alkaloids: The potential increase in plasma concentrations of ergot alkaloids when coadministered with ketoconazole tablets may increase the risk of ergotism, i.e., a risk for vasospasm potentially leading to cerebral ischemia and/or ischemia of the extremities. Eletriptan: Eletriptan should be used with caution with ketoconazole, and specifically, should not be used within at least 72 hours of treatment with ketoconazole
Antineoplastics | irinotecan | dasatinib, lapatinib, nilotinib | bortezomib, busulphan, docetaxel, erlotinib, imatinib, ixabepilone, paclitaxel, trimetrexate, vinca alkaloids | Irinotecan: The potential increase in plasma concentrations of irinotecan when coadministered with ketoconazole tablets may increase the risk of potentially fatal adverse events. Docetaxel: In the presence of ketoconazole, the clearance of docetaxel in cancer patients was shown to decrease by 50%.
Antipsychotics, Anxiolytics and Hypnotics | Lurasidone, alprazolam, oral midazolam, pimozide, triazolam |  | aripiprazole, buspirone, haloperidol, midazolam IV, quetiapine, ramelteon, risperidone | The increase in plasma concentrations of lurasidone when coadministered with ketoconazole tablets may increase the risk of serious side effects (See CONTRAINDICATIONS). Alprazolam, midazolam, triazolam: Coadministration of ketoconazole tablets with oral midazolam or triazolam, or alprazolam may cause several-fold increases in plasma concentrations of these drugs. This may potentiate and prolong hypnotic and sedative effects, especially with repeated dosing or chronic administration of these agents. Pimozide: The potential increase in plasma concentrations of pimozide when coadministered with ketoconazole tablets may increase the risk of serious cardiovascular events including QT prolongation and torsade de pointes. Aripiprazole: Coadministration of ketoconazole (200 mg/day for 14 days) with a 15 mg single dose of aripiprazole increased the AUC of aripiprazole and its active metabolite by 63% and 77%, respectively. The effect of a higher ketoconazole dose (400 mg/day) has not been studied. When ketoconazole is given concomitantly with aripiprazole, the aripiprazole dose should be reduced to one-half of the recommended dose. Buspirone: Ketoconazole is expected to inhibit buspirone metabolism and increase plasma concentrations of buspirone. If a patient has been titrated to a stable dosage on buspirone, a dose reduction of buspirone may be necessary to avoid adverse events attributable to buspirone or diminished anxiolytic activity.
Antivirals |  |  | indinavir, maraviroc, saquinavir
Beta Blockers |  |  | nadolol
Calcium Channel Blockers | felodipine, nisoldipine |  | other dihydropyridines, verapamil | Calcium channel blockers can have a negative inotropic effect which may be additive to those of ketoconazole. The potential increase in plasma concentrations of calcium channel blockers when coadministered with ketoconazole tablets may increase the risk of edema and congestive heart failure. Dihydropyridines: Concomitant administration of ketoconazole tablets may cause several-fold increases in plasma concentrations of dihydropyridines
Cardiovascular Drugs, Miscellaneous | ranolazine |  | aliskiren, bosentan | Ranolazine: The potential increase in plasma concentrations of ranolazine when coadministered with ketoconazole tablets may increase the risk of serious cardiovascular events including QT prolongation. Bosentan: Coadministration of bosentan 125 mg twice daily and ketoconazole, increased the plasma concentrations of bosentan by approximately 2 fold in normal volunteers. No dose adjustment of bosentan is necessary, but patients should be monitored for increased pharmacologic effects and adverse reactions of bosentan.
Diuretics | eplerenone |  |  | The potential increase in plasma concentrations of eplerenone when coadministered with ketoconazole tablets may increase the risk of hyperkalemia and hypotension.
Gastrointestinal Drugs | cisapride |  | aprepitant | Cisapride: Oral ketoconazole potently inhibits the metabolism of cisapride resulting in a mean eight-fold increase in AUC of cisapride, which can lead to serious cardiovascular events including QT prolongation.
Immunosuppressants |  | everolimus, rapamycin (also known as sirolimus), temsirolimus | budesonide, ciclesonide, cyclosporine, dexamethasone, fluticasone, methylprednisolone, tacrolimus | Rapamycin (sirolimus): Ketoconazole tablets 200 mg daily for 10 days increased the Cmax and AUC of a single 5 mg dose of sirolimus by 4.3 fold and 10.9 fold, respectively in 23 healthy subjects. Fluticasone: Coadministration of fluticasone propionate and ketoconazole is not recommended unless the potential benefit to the patient outweighs the risk of systemic corticosteroid side effects.
Lipid Regulating Drugs | lovastatin, simvastatin |  | atorvastatin | The potential increase in plasma concentrations of atorvastatin, lovastatin and simvastatin when coadministered with ketoconazole tablets may increase the risk of skeletal muscle toxicity, including rhabdomyolysis.
Respiratory Drugs |  | salmeterol
Urological Drugs |  |  | fesoterodine, sildenafil, solifenacin, tadalafil, tolterodine, vardenafil | Vardenafil: A single dose of 5 mg of vardenafil should not be exceeded when coadministered with ketoconazole.
Other | colchicine, in subjects with renal or hepatic impairment; tolvaptan | colchicine | alcohol, cinacalcet | Colchicine: The potential increase in plasma concentrations of colchicine when coadministered with ketoconazole tablets may increase the risk of potentially fatal adverse events Tolvaptan: Ketoconazole 200 mg administered with tolvaptan increased tolvaptan exposure by 5 fold. Larger doses would be expected to produce larger increases in tolvaptan exposure. There is not adequate experience to define the dose adjustment that would be needed to allow safe use of tolvaptan with strong CYP3A inhibitors such as ketoconazole. Alcohol: Exceptional cases have been reported of a disulfiram-like reaction to alcohol, characterized by flushing, rash, peripheral edema, nausea and headache. All symptoms completely resolved within a few hours.

Carcinogenesis, Mutagenesis, Impairment of Fertility

Ketoconazole did not show any signs of mutagenic potential when evaluated using the dominant lethal mutation test or the Ames Salmonella microsomal activator assay. Ketoconazole was not carcinogenic in an 18 month, oral study in Swiss albino mice or a 24 month oral carcinogenicity study in Wistar rats at dose levels of 5, 20 and 80 mg/kg/day. The high dose in these studies was approximately 1x (mouse) or 2x (rat) the clinical dose in humans based on a mg/m^2 comparison.

Pregnancy

Teratogenic effects

Ketoconazole has been shown to be teratogenic (syndactylia and oligodactylia) in the rat when given in the diet at 80 mg/kg/day (2 times the maximum recommended human dose, based on body surface area comparisons). However, these effects may be related to maternal toxicity, evidence of which also was seen at this and higher dose levels.

There are no adequate and well controlled studies in pregnant women. Ketoconazole tablets should be used during pregnancy only if the potential benefit justifies the potential risk to the fetus.

Nonteratogenic Effects

Ketoconazole has also been found to be embryotoxic in the rat when given in the diet at doses higher than 80 mg/kg during the first trimester of gestation.

In addition, dystocia (difficult labor) was noted in rats administered oral ketoconazole during the third trimester of gestation. This occurred when ketoconazole was administered at doses higher than 10 mg/kg (about one fourth the maximum human dose, based on body surface area comparison).

Nursing Mothers

Ketoconazole has been shown to be excreted in the milk. Mothers who are under treatment with ketoconazole tablets should not breast feed.

Pediatric Use

Ketoconazole tablets have not been systematically studied in children of any age, and essentially no information is available on children under 2 years. Ketoconazole tablets should not be used in pediatric patients unless the potential benefit outweighs the risks.

ADVERSE REACTIONS

Because clinical trials are conducted under widely varying conditions, adverse reaction rates observed in the clinical trials of a drug cannot be directly compared to rates in the clinical trials of another drug and may not reflect the rates observed in practice.

The following adverse reactions were reported in clinical trials:

Immune System Disorders: anaphylactoid reaction

Endocrine Disorders: gynecomastia

Metabolism and Nutrition Disorders: alcohol intolerance, anorexia, hyperlipidemia, increased appetite

Psychiatric Disorders: insomnia, nervousness

Nervous System Disorders: headache, dizziness, paresthesia, somnolence

Eye Disorders: photophobia

Vascular Disorders: orthostatic hypotension

Respiratory, Thoracic and Mediastinal Disorders: epistaxis

Gastrointestinal Disorders: vomiting, diarrhea, nausea, constipation, abdominal pain, abdominal pain upper, dry mouth, dysgeusia, dyspepsia, flatulence, tongue discoloration

Hepatobiliary Disorders: hepatitis, jaundice, hepatic function abnormal

Skin and Subcutaneous Tissues Disorders: erythema multiforme, rash, dermatitis, erythema, urticaria, pruritus, alopecia, xeroderma

Musculoskeletal and Connective Tissue Disorders: myalgia

Reproductive System and Breast Disorders: menstrual disorder

General Disorders and Administration Site Conditions: asthenia, fatigue, hot flush, malaise, edema peripheral, pyrexia, chills

Investigations: platelet count decreased.

Postmarketing Experience

The following adverse reactions have been identified during postapproval use of ketoconazole tablets. Because these reactions are reported voluntarily from a population of uncertain size, it is not always possible to reliably estimate their frequency or establish a causal relationship to drug exposure.

The following adverse reactions were reported during postmarketing experience:

Blood and Lymphatic System Disorders: thrombocytopenia

Immune System Disorders: allergic conditions including anaphylactic shock, anaphylactic reaction, angioneurotic edema

Endocrine Disorders: adrenocortical insufficiency

Nervous System Disorders: reversible intracranial pressure increased (e.g., papilloedema, fontanelle bulging in infants)

Hepatobiliary Disorders: serious hepatotoxicity including hepatitis cholestatic, biopsy-confirmed hepatic necrosis, cirrhosis, hepatic failure including cases resulting in transplantation or death

Skin and Subcutaneous Tissue Disorders: acute generalized exanthematous pustulosis, photosensitivity

Musculoskeletal and Connective Tissue Disorders: arthralgia

Reproductive System and Breast Disorders: erectile dysfunction; with doses higher than the recommended therapeutic dose of 200 or 400 mg daily, azoospermia.

OVERDOSAGE

In the event of acute accidental overdose, treatment consists of supportive and symptomatic measures. Within the first hour after ingestion, activated charcoal may be administered.

DOSAGE AND ADMINISTRATION

There should be laboratory as well as clinical documentation of infection prior to starting ketoconazole therapy. The usual duration of therapy for systemic infection is 6 months. Treatment should be continued until active fungal infection has subsided.

Adults

The recommended starting dose of ketoconazole tablets is a single daily administration of 200 mg (one tablet). If clinical responsiveness is insufficient within the expected time, the dose of ketoconazole tablets may be increased to 400 mg (two tablets) once daily.

Children

In small numbers of children over 2 years of age, a single daily dose of 3.3 to 6.6 mg/kg has been used. Ketoconazole tablets have not been studied in children under 2 years of age.

HOW SUPPLIED

Each ketoconazole tablet USP contains ketoconazole, USP 200 mg available in bottles of 100 (NDC 64380-827-06) and 500 (NDC 64380-827-07). The tablets are white to off white, round shaped flat-beveled debossed with "S" and "500" on the scored side and plain on the other side.

Store at 20° to 25° C (68° to 77° F) [see USP Controlled Room Temperature].

Protect from moisture.

Keep this and all medications out of reach of children.

Manufactured by:

Strides Pharma Science Limited

Puducherry - 605014, India.

Distributed by:

Strides Pharma Inc,

Bridgewater, NJ 08807

Revised: 07/2025

MEDICATION GUIDE

KETOCONAZOLE (KEE-toe-KON-a-zole) TABLETS USP

What is the most important information I should know about ketoconazole tablets?

Ketoconazole tablets are not the only medicine available to treat fungal infections and should only be used when other medicines are not right for you. Talk to your healthcare provider to find out if ketoconazole tablets are right for you.

Ketoconazole tablets can cause serious side effects, including:

- liver problems (hepatotoxicity). Some people who were treated with ketoconazole the active ingredient in ketoconazole tablets, had serious liver problems that led to death or the need for a liver transplant. Call your healthcare provider right away if you have any of the following symptoms:
- loss of appetite or start losing weight (anorexia)
- nausea or vomiting
- feel tired
- stomach pain or tenderness
- dark urine or light colored stools
- yellowing of your skin or the whites of your eyes
- fever or rash

- changes in the electrical activity of your heart called QT prolongation. QT prolongation can cause irregular heart beats that can be life threatening.This can happen when ketoconazole tablets are taken with certain medicines, such as dofetilide, quinidine, pimozide, lurasidone, cisapride, methadone, disopyramide, dronedarone, and ranolazine. Talk to your healthcare provider about other medicines you are taking before you start taking ketoconazole tablets. Tell your healthcare provider right away if you feel faint, lightheaded, dizzy, or feel your heart beating irregularly or fast. These may be symptoms related to QT prolongation.

What are ketoconazole tablets?

- Ketoconazole tablets are prescription medicine used to treat serious fungal infections including: blastomycosis, coccidioidomycosis, histoplasmosis, chromomycosis, and paracoccidioidomycosis.
- Ketoconazole tablets are not for people with fungal nail infections.
- Ketoconazole tablets have not been approved for the treatment of advanced prostate cancer or Cushing's syndrome. The safety and efficacy have not been established.
- Ketoconazole tablets should only be used in children if prescribed by the healthcare provider who has determined that the benefits outweigh the risks.

Who should not take ketoconazole tablets?

- Do not take ketoconazole tablets if you:
- have liver problems
- take lurasidone. Taking ketoconazole tablets with this medicine may increase the risk of serious side effects.
- take simvastatin, or lovastatin. Ketoconazole tablets when taken with these medicines may cause muscle problems.
- take eplerenone, dihydroergotamine, ergotamine, ergometrine (ergonovine), methylergometrine (methylergonovine) or nisoldipine.
- take triazolam, midazolam, or alprazolam. Taking ketoconazole tablets with these medicines may make you very drowsy and make your drowsiness last longer.
- are allergic to ketoconazole or any of the ingredients in ketoconazole tablets. See the end of this Medication Guide for a complete list of ingredients in ketoconazole tablets.

Before you take ketoconazole tablets, tell your healthcare provider if you:

- have had an abnormal heart rhythm tracing (ECG) or anyone in your family have or have had a heart problem called "congenital long QT syndrome".
- have adrenal insufficiency.
- are pregnant or plan to become pregnant. It is not known if ketoconazole tablets will harm your unborn baby.
- are breastfeeding or plan to breastfeed. Ketoconazole can pass into your breast milk. You and your healthcare provider should decide if you will take ketoconazole tablets or breastfeed. You should NOT do both.

Tell your healthcare provider about all the medicines you take, including prescription and over-the-counter medicines, vitamins, and herbal supplements.

Using ketoconazole tablets with certain other medicines may affect each other. Using ketoconazole tablets with other medicines can cause serious side effects.

How should I take ketoconazole tablets?

- Take ketoconazole tablets 1 time each day.
- Do not stop taking ketoconazole tablets without first talking to your healthcare provider.

What should I avoid while taking ketoconazole tablets?

- Do not drink alcohol while taking ketoconazole tablets.

What are the possible side effects of ketoconazole tablets?

Ketoconazole tablets may cause serious side effects, including:

- See "What is the most important information I should know about ketoconazole tablets?"
- adrenal insufficiency. Adrenal insufficiency is a condition in which the adrenal glands do not make enough steroid hormones. Ketoconazole tablets may cause adrenal insufficiency if you take a high dose. Your healthcare provider will follow you closely if you have adrenal insufficiency or if you are taking prednisone or other similar medicines for long periods of time. Call your healthcare provider right away if you have symptoms of adrenal insufficiency such as tiredness, weakness, dizziness, nausea, and vomiting.
- serious allergic reactions. Some people can have a serious allergic reaction to ketoconazole tablets. Stop taking ketoconazole tablets and go to the nearest hospital emergency room right away if you get a rash, itching, hives, fever, swelling of the lips or tongue, chest pain, or have trouble breathing. These could be signs of a serious allergic reaction.
- muscle problems. Taking certain medicines with ketoconazole tablets may cause muscle problems. See "Who should not take ketoconazole tablets?"

The most common side effects of ketoconazole tablets include nausea, headache, diarrhea, stomach pain, and abnormal liver function tests.

These are not all the possible side effects of ketoconazole tablets. For more information, ask your healthcare provider or pharmacist.

Call your doctor for medical advice about side effects. You may report side effects to FDA at 1-800- FDA-1088.

How should I store ketoconazole tablets?

- Store ketoconazole tablets at room temperature between 68° and 77° F (20° and 25° C)
- Keep ketoconazole tablets dry.

General information about the safe and effective use of ketoconazole tablets.

Medications are sometimes prescribed for purposes other than those listed in a Medication Guide. Do not use ketoconazole tablets for a condition for which they were not prescribed. Do not give ketoconazole tablets to other people, even if they have the same symptoms that you have. They may harm them.

This Medication Guide summarizes the most important information about ketoconazole tablets.

If you would like more information, talk to your healthcare provider. You can ask your pharmacist or healthcare provider for information about ketoconazole tablets that is written for health professionals.

What are the ingredients in ketoconazole tablets, USP?

Active ingredient: ketoconazole, USP

Inactive ingredients: colloidal silicon dioxide, corn starch, lactose monohydrate, magnesium stearate, microcrystalline cellulose, and povidone.

This Medication Guide has been approved by the U.S. Food and Drug Administration.

Manufactured by:

Strides Pharma Science Limited

Puducherry - 605014, India.

Distributed by:

Strides Pharma Inc,

Bridgewater, NJ 08807

Revised: 07/2025